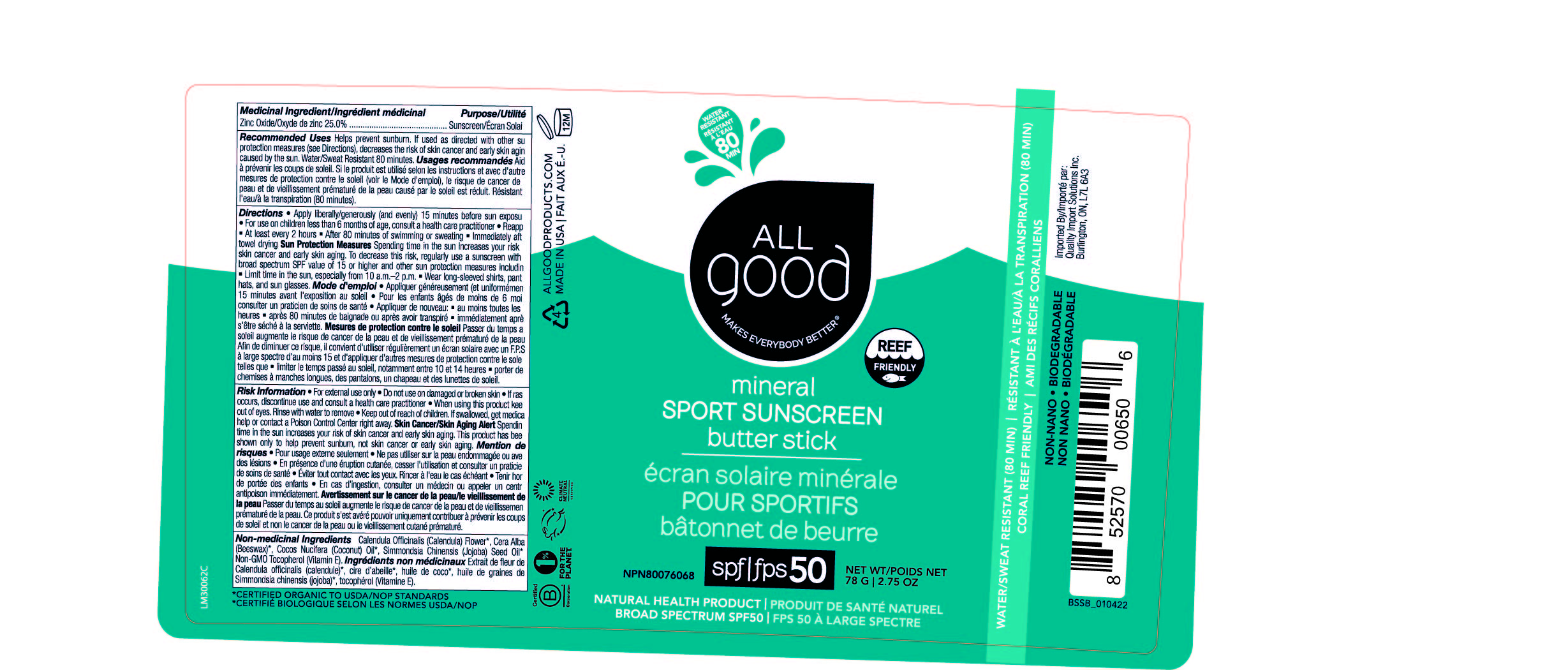 DRUG LABEL: All Good Mineral Sport Sunscreen Butter Stick SPF 50
NDC: 75786-239 | Form: OINTMENT
Manufacturer: Elemental Herbs, Inc.
Category: otc | Type: HUMAN OTC DRUG LABEL
Date: 20250505

ACTIVE INGREDIENTS: ZINC OXIDE 25 g/100 g
INACTIVE INGREDIENTS: COCONUT OIL; TOCOPHEROL; CALENDULA OFFICINALIS FLOWER; WHITE WAX; JOJOBA OIL

92204 All Good Mineral Sport Sunscreen Butter Stick SPF 50 (Bilingual Canada Label)

ACTIVE INGREDIENT

Medicinal ingredient/Ingrédient médicinal:Zinc Oxide/Oxyde de zinc 25 %

Purpose/Utilité

Sunscreen/Écran Solai

Recommended UsesHelps prevent sunburn. If used as directed with other sun protection measures (see Directions), decreases the risk of skin cancer and early skin aging caused by the sun. Water/Sweat Resistant 80 minutes.

Usages recommandésAide a prévenir les coups de soleil. Si le produit est utilisé selon les instructions et avec d'autres mesures de protection contre le oleil [voir le Mode d'emploi], le risque de cancer de la peau et de viellissement prématuré de la peau causé par le soleil est réduit. Résistant l'eau/à la transpiration (80 minutes).

Directions

- Apply liberally/generously (and evenly) 15 minutes before sun exposure
- For use on children less than 6 months of age, consult a health care practitioner
- Reapply
- At least every 2 hours
- After 80 minutes of swimming or sweating
- Immediately after towel drying

Mode d'emploi

- Appliquer généreusement (et uniformément) 15 minutes avant l'exposition au soleil
- Pour les enfants agés de moins de 6 mois, consulter un praticien de soins de santé
- Appliquer denouveau:
- au moins toutes les 2 heures
- aprés 80 minutes de baignade ou aprés avoir transpiré
- Immediatement apres s'etre séché a la serviette.

INDICATIONS AND USAGE

Sun Protection MeasuresSpending time in the sun increases your risk of skin cancer and early skin aging. To decrease this risk, regularly use a sunscreen with a broad spectrum SPF value of 15 or higher and other sun protection measures including

- Limit time in the sun, especially from 10 a.m.-2 p.m.
- Wear long-sleeved shirts, pants, hats, and sun glasses.

Mesures de protection contre le soleilPasser du temps au soleil augmente le risque de cancer de la peau et de vieillissement prématuré de la peau. Afin de diminuer ce risque, il convient d'utiliser réeguliérement un écran solaire avec un F.P.S. a large spectre d'au moins 15 et d'appliquer d'autres mesures de protection contre le soleil, telles que

- limiter le temps passé au soleil notamment entre 10 et 14 heures
- porter des chemises a manches longues, des pantalons, un chapeau et des lunettes de soleil.

WARNINGS

Risk InformationFor external use only

Mention de risquesPour usage externe seulement

Do not use on damaged or broken skin.

Ne pas utiliser sur la peau endommagée ou avec des lésions

STOP USE

If rash occurs, discontinue use and consult a health care practitioner.

En présence d'une éruption cutanée, cesser l'utilisation et consulter un praticien de soins de santé

When using this product keep out of eyes. Rinse with water to remove.

Eviter tout contact avec les yeux. Rincer a l'eau le cas échéant

- Keep out of reach of children. If swallowed, get medical help or contact a Poison Control Center right away.
- Tenir hors de portée des enfants
- En cas d'ingestion, consulter un médecin ou appeler un centre antipoison immédiatement.

OTHER SAFETY INFORMATION

Skin Cancer/Skin Aging AlertSpending time in the sun increases your risk of skin cancer and early skin aging. This product has been shown only to help prevent sunburn, not skin cancer or early skin aging.

Avertissement sur le cancer de la peau/le vieillissement de la peauPasser du temps au soleil augmente le risque de concer de la peau et de vieillissement prématuré de la peau. Ce produit s'est avéré pouvoir uniquement contribuer a prévenir les coups de soleil et non le cancer de la peau ou le viellissement cutané prématuré.

INACTIVE INGREDIENT

Non-medicinal ingredientsCalendula Officinalis (Calendula) Flower*, Cera Alba (Beeswax)* ,Cocos Nucifera (Coconut) Oil*, Simmondsia Chinensis (Jojoba) Seed Oil*, Non-GMO Tocopherol (Vitamin E.)

Ingrédients non médicinauxExtrait de fleur de Calendula officinalis (calendule)*, cire d'abeille* ,huile de coco*, huile de graines de Simmondsia chinensis (jojoba)*, tocophérol (Vitamine E).

* CERTIFIED ORGANIC TO USDA/NOP STANDARDS

*CERTIFIÉ BIOLOGIQUE SELON LES NORMES USDA/NOP

QUESTIONS

QuestionAll Good, PO Box 203, Morro Bay, CA 93443

ALL GOOD

mineral SPORT SUNSCREEN butter STICK

écran solaire minérale POUR SPORTIFS bâtonnet de beurre

NPN80076068

spf|fps50

NET WT/POIDS NET 2.75 OZ | 78 G

NATURAL HEALTH PRODUCT | PRODUIT DE SANTE NATUREL

BROAD SPECTRUM SPF50 | FPS50 À LARGE SPECTRE

WATER/SWEAT RESISTANT (80 MIN) | RÉSISTANT À L'EAU/À LA TRANSPIRATION (80 MIN)

CORAL REEF FRIENDLY | AMI DES RÉCIFS CORALLIENS

NON-NANO

- BIODEGRADABLE

NON NANO

- BIODEGRADABLE

ALLGOODPRODUCTS.COM

MADE IN USA | FAIT AUX E.-U.

Imported by/Importe par:

Quality Import Solutions Inc.,

Burlington, ON, L7L 6A3